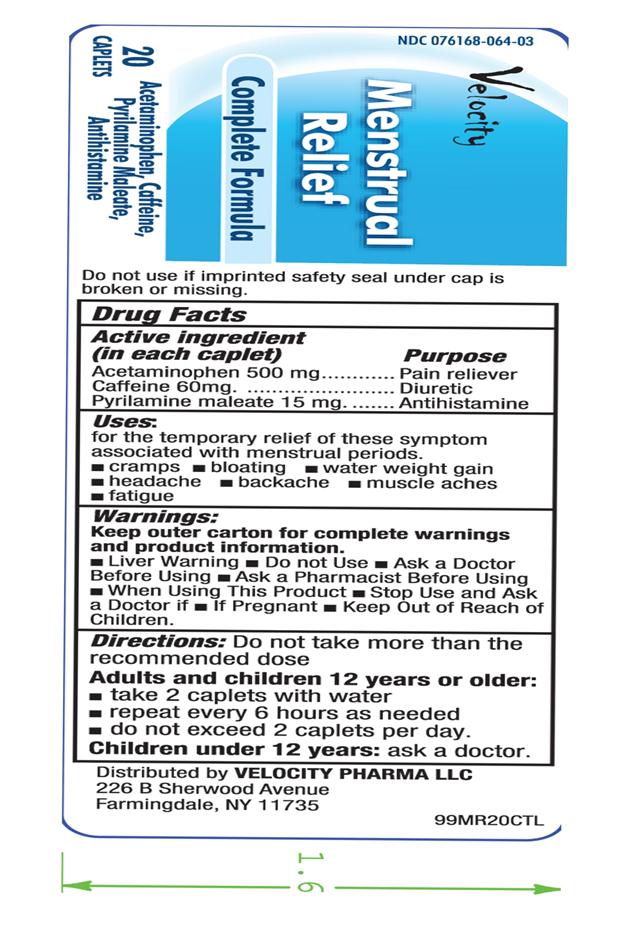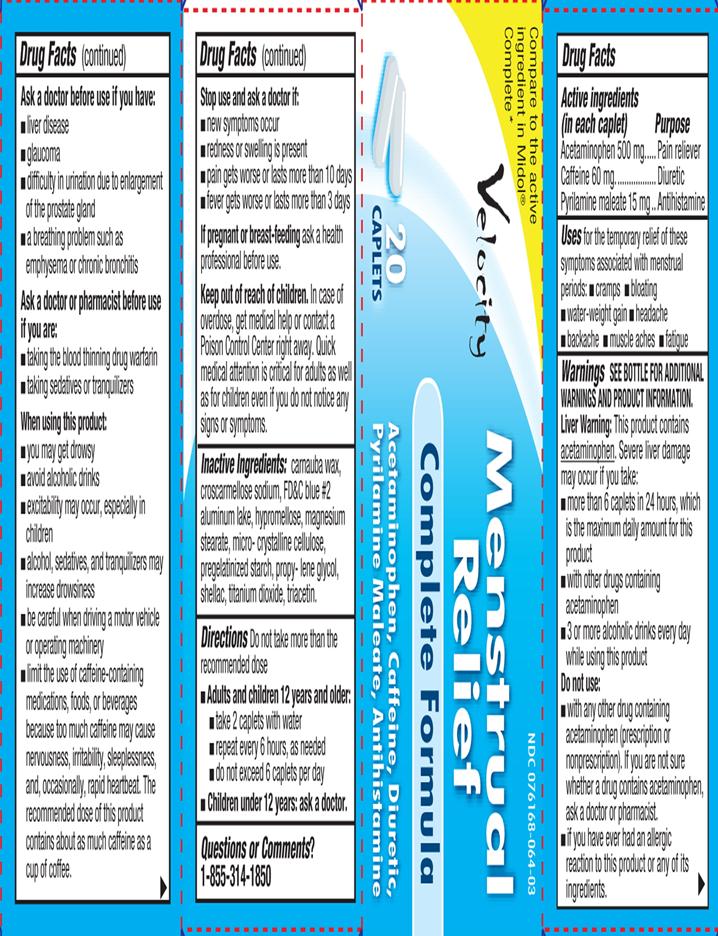 DRUG LABEL: Menstrual Relief
NDC: 76168-064 | Form: TABLET
Manufacturer: Velocity Pharma
Category: otc | Type: HUMAN OTC DRUG LABEL
Date: 20131023

ACTIVE INGREDIENTS: ACETAMINOPHEN 500 mg/1 1; CAFFEINE 60 mg/1 1; PYRILAMINE MALEATE 15 mg/1 1
INACTIVE INGREDIENTS: CARNAUBA WAX; CROSCARMELLOSE SODIUM; FD&C BLUE NO. 2; HYPROMELLOSES; MAGNESIUM STEARATE; CELLULOSE, MICROCRYSTALLINE; STARCH, CORN; PROPYLENE GLYCOL; SHELLAC; TITANIUM DIOXIDE; TRIACETIN

Acetaminophen, Caffeine, Diuretic, Pyrilamine Maleate, Antihistamine

Active Ingredient

(in each caplet)

Acetaminophen 500 mg

Caffeine 60 mg

Pyrilamine Maleate 15 mg

Purpose

Pain Reliever

Diuretic

Antihistamine

Uses

For the temporary relief of these symptoms associated with menstrual periods:

- Cramps
- Bloating
- Water-weight gain
- Headache
- Backache
- Muscle aches
- Fatigue

Warnings

SEE BOTTLE FOR ADDITIONAL WARNINGS AND PRODUCT INFORMATION.

Liver Warning: This product contains acetaminophen. Severe liver damage may occur if you take:

- More than 6 caplets in 24 hours, which is the maximum daily amount for this product
- With other drug containing acetaminophen
- 3 or more alcoholic drinks every day while using this product

Do not use:

- With any other drug containing acetaminophen (prescription or nonprescription). If you are not sure whether a drug contains acetaminophen, ask a doctor or pharmacist.
- If you have ever had an allergic reaction to this product or any of its ingredients.

Ask a doctor before use if you have:

- Liver disease
- Glaucoma
- Difficulty in urination due to enlargement of the prostate gland
- A breathing problem such as emphysema or chronic bronchitis

Ask a doctor or pharmacist before use if you are:

- Taking the blood thinning drug warfarin
- Taking sedatives or tranquilizers
  When using this product:
- You may get drowsy
- Avoid alcoholic drinks
- Excitability may occur, especially in children
- Alcohol, sedatives, and tranquilizers may increase drowsiness
- Be careful when driving a motor vehicle or operating machinery
- Limit the use of caffeine-containing medications, foods, or beverages because too much caffeine may cause nervousness, irritability, sleeplessness, and occasionally, rapid heartbeat. The recommended dose of this product contains as a cup of coffee.
  Stop use and ask a doctor if:
- new symptoms occur
- redness or swelling is present
- pain gets worse or lasts more than 10 days
- fever gets worse or lasts more than 3 days

If pregnant or breast feeding ask a health professional before use.

Keep out of reach of children.

In case of overdose, get medical help or contact a Poison Control Center right away. Quick medical attention is critical for adults as well as for children even if you do not notice any signs or symptoms.

Directions

Do not take more than the recommended dose

- Adults and Children 12 years and older:
- take 2 caplets with water
- repeat every 6 hours, as needed
- do not exceed 6 caplets per day
- Children under 12 years: ask a doctor.

Other Information

- Store at a controlled temperature between 62 and 77 degrees F

Inactive Ingredients

Carnauba wax, croscarmellose sodium, FD&C blue #2 aluminum lake, hypromellose, magnesium stearate, micro-crystalline cellulose, pregelatinized starch, propylene glycol, shellac, titanium dioxide, triacetin

Questions?

Call 1-855-314-1850

TAMPER EVIDENT: DO NOT USE IF IMPRINTED SAFETY SEAL UNDER CAP IS BROKEN OR MISSING

Distributed by: Velocity Pharma LLC

PACKAGE LABEL.PRINCIPAL DISPLAY PANEL

NDC: 76168-064-03 –20 COUNT

Enteric Coated to help prevent upset stomach